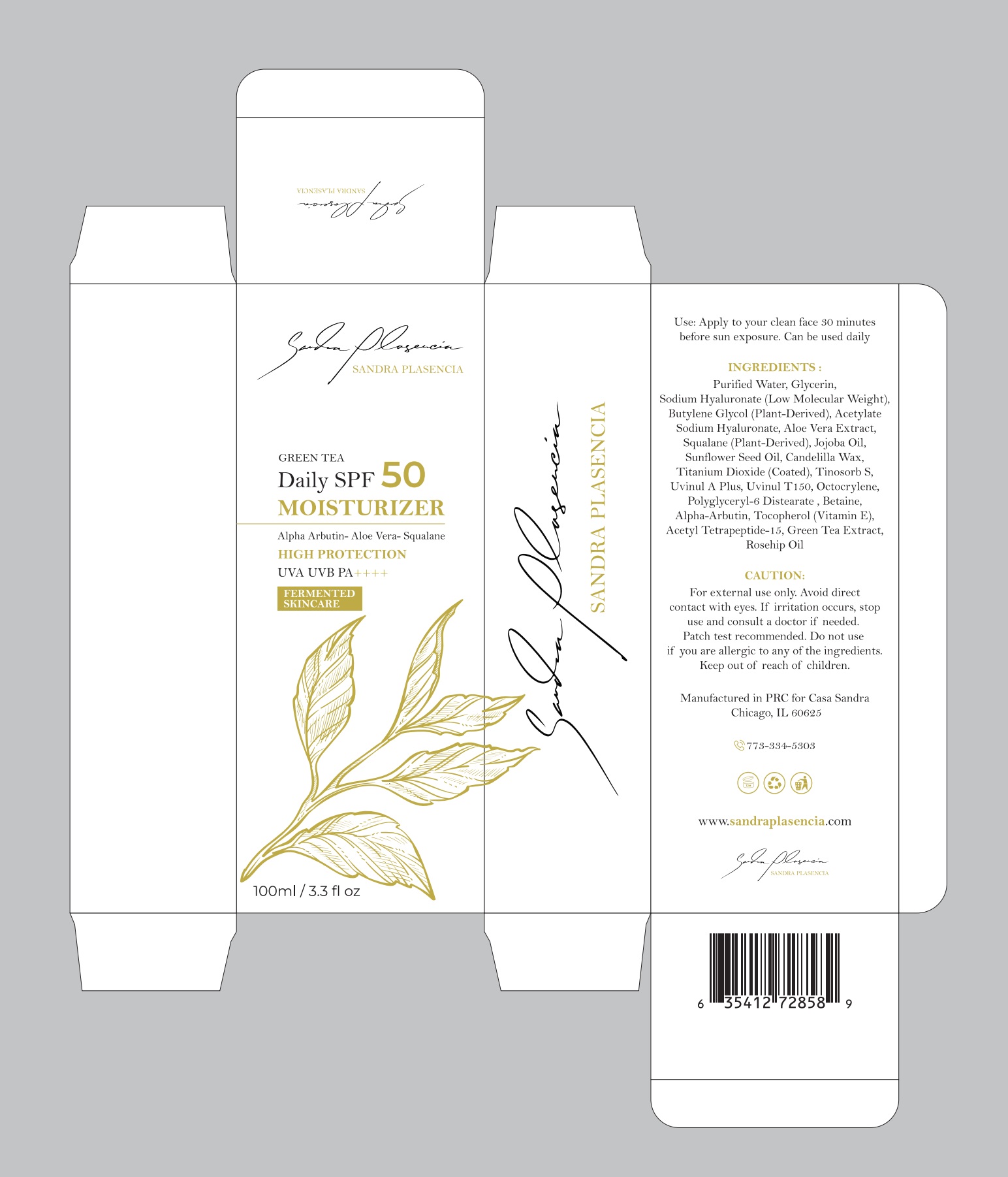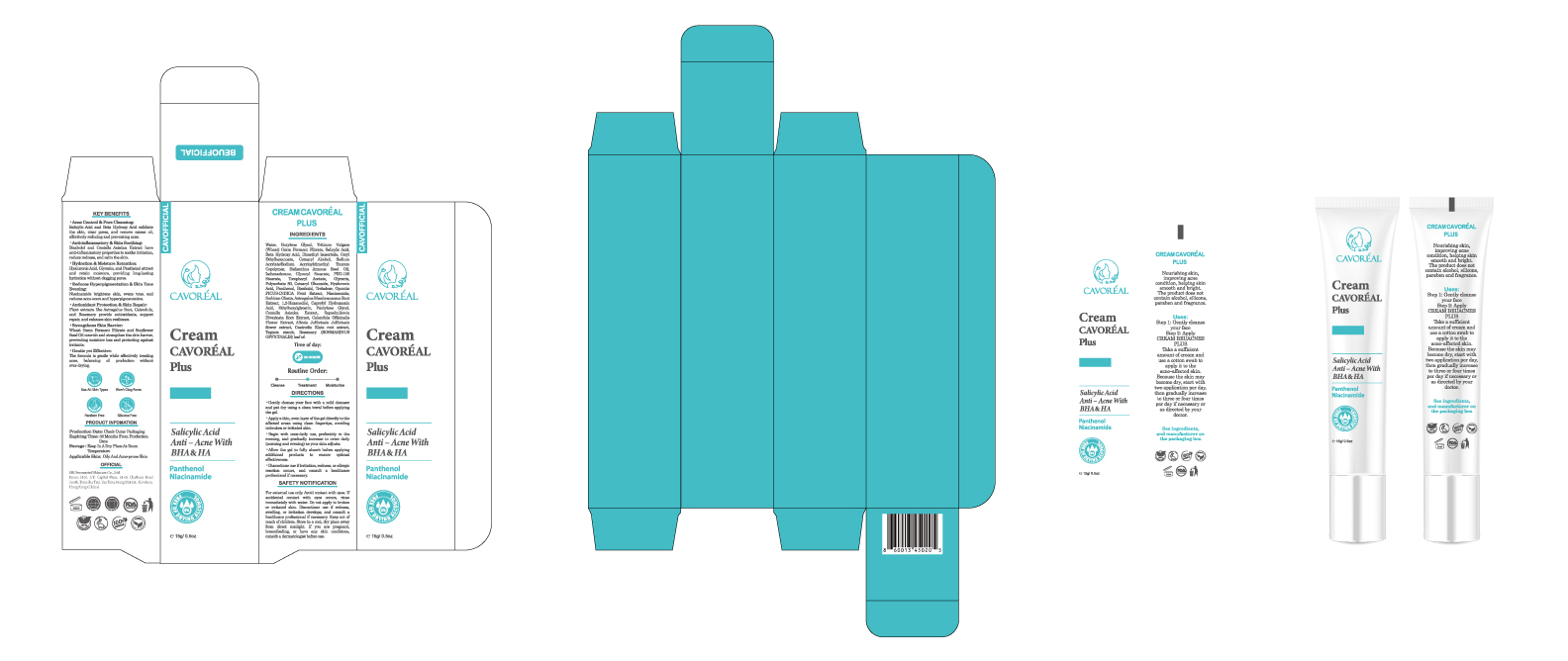 DRUG LABEL: CAVOREAL Plus Salicylic Acid Anti Acne with BHA HA
NDC: 87036-032 | Form: CREAM
Manufacturer: Guangzhou Meijiao Medical Biotechnology Co., Ltd.
Category: otc | Type: HUMAN OTC DRUG LABEL
Date: 20251120

ACTIVE INGREDIENTS: SALICYLIC ACID 1 g/15 mL
INACTIVE INGREDIENTS: ASTRAGALUS MEMBRANACEUS ROOT POWDER; SORBITAN OLEATE; 1,2-HEXANEDIOL; TAPIOCA STARCH; DIMETHYL ISOSORBIDE; CENTELLA ASIATICA; WATER O-15; TRITICUM VULGARE (WHEAT) GERM; BUTYLENE GLYCOL; ALFUZOSIN HYDROXY ACID; CETYL ETHYLHEXANOATE; CETEARYL ALCOHOL; HYDROXYETHYL ACRYLATE/SODIUM ACRYLOYLDIMETHYL TAURATE COPOLYMER (45000 MPA.S AT 1%); HELIANTHUS ANNUUS (SUNFLOWER) SEED OIL; ISOHEXADECANE; GLYCERYL STEARATE; PEG-100 STEARATE; GLYCERIN; POLYSORBATE 80; HYALURONIC ACID; PANTHENOL; BISABOLOL; TREHALOSE; OPUNTIA FICUS-INDICA; NIACINAMIDE; SAPOSHNIKOVIA DIVARICATA ROOT; ETHYLHEXYLGLYCERIN; ALBIZIA JULIBRISSIN FLOWER; GASTRODIA ELATA TUBER; CALENDULA OFFICINALIS FLOWER; PENTYLENE GLYCOL; ROSMARINUS OFFICINALIS (ROSEMARY) LEAF OIL; CAPRYLHYDROXAMIC ACID

Fermented Fast Acne Removal Gel Blemish Clogged Pores Oil Control Sensitive Skin Soothing Herbal Anti Bacteria Pimple Acne Cream

ACTIVE INGREDIENT

INACTIVE INGREDIENT

INGREDIENTS
Purified Water, Glycerin,Sodium Hyaluronate (Low Molecular Weight),Butylene Glycol (Plant-Derived), AcetylateSodium Hyaluronate, Aloe Vera Extract,Squalane (Plant-Derived), Jojoba Oil,Sunflower Seed Oil, Candelilla Wax,Titanium Dioxide (Coated), Tinosorb S,Uvinul A Plus, Uvinul T150, Octocrylene,Polyglyceryl-6 Distearate , Betaine,Alpha-Arbutin, Tocopherol (Vitamin E),Acetyl Tetrapeptide-15, Green Tea Extract,Rosehip Oil

PURPOSE

Alpha Arbutin- Aloe Vera- SqualaneHIGH PROTECTIONUVA UVB PA++++
FERMENTEDSKINCARE

WARNINGS

CAUTION:
For external use only. Avoid directcontact with eyes. If irritation occurs, stopuse and consult a doctor if needed.Patch test recommended. Do not useif you are allergic to any of the ingredients.Keep out of reach of children.

DO NOT USE

CAUTION:
For external use only, Avoid direct contact with eyes.If irritation occurs, stop use and consult a doctor if needed,Patch test recommended.Do not use if you are allergic to any of the ingredients.Keep out of reach of children.

KEEP OUT OF REACH OF CHILDREN

CAUTION:
For external use only. Avoid directcontact with eyes. If irritation occurs, stop useand consult a doctor if needed.Patch test recommended.Do not use if you are allergic to any of theingredients.Keep out of reach of children.

STOP USE

CAUTION:
For external use only, Avoid direct contact with eyes.If irritation occurs, stop use and consult a doctor if needed,Patch test recommended.Do not use if you are allergic to any of the ingredients.Keep out of reach of children.

INDICATIONS AND USAGE

Use: Apply to your clean face 30 minutesbefore sun exposure. Can be used daily

WHEN USING

Use: Apply to your clean face 30 minutesbefore sun exposure. Can be used daily

DOSAGE AND ADMINISTRATION

Use: Apply to your clean face 30 minutesbefore sun exposure. Can be used daily

PACKAGE LABEL

Use: Apply to your clean faee $o minutesbelore sun exposure, can bse used daily
SANDRA PLASENCIA
GREEN TEADaily SPF 5O
MOISTURIZER
Alpha Arbutin- Aloe Wern-SqualaneHIGH PROTECTION
UVA UVB PA++++
FERMENTED
SHINCARE
VIONISVId VHGNVS
INGREDIENTS :
Purified water, lycerin.Sodium Hvaluronate (Low Mlolecular weight).Butylemne Glyeol (Plant-Derived), AcetylaceSodium Hylummate, Aloe Vera Exerace,Squalane(Plant crived) JojobCl.Sunikwer Seed 0il, ('andelilla wax,Titanium Dioxide (oatel], inosorb S,UvinulA Pus,UviuTT150,OccocryinePolyglyeeryl-6 Distearate . Betaine,Alpls-Arbuun, Tocopberol (Vitamin E).Acetyl"letrpeptide.16,(iren 'ea Extract,Raschip Cl
CAUTION:
For external use only Avoid directcotact with eves,If irritatmm occurs, stopuse and consult a doctor if msled.putch test recommicnded. J)o not useif wi are alkrgic to any ofthe ingredients.kecp out of reach of children.
Mamunctured in PRc f casa SandrnChicage,[l.60625
0778-854-590$
www.sandraplasencia.com